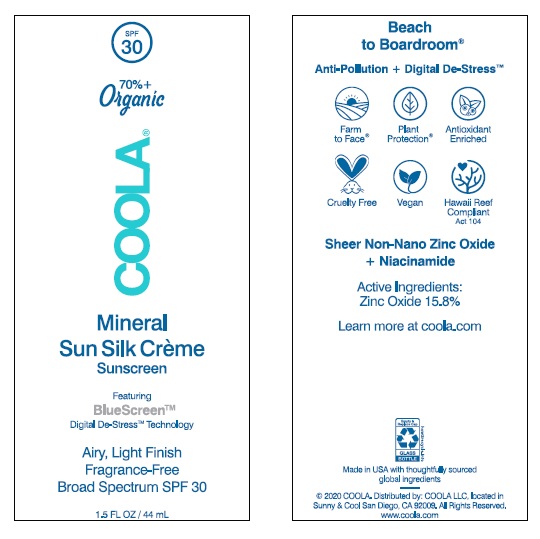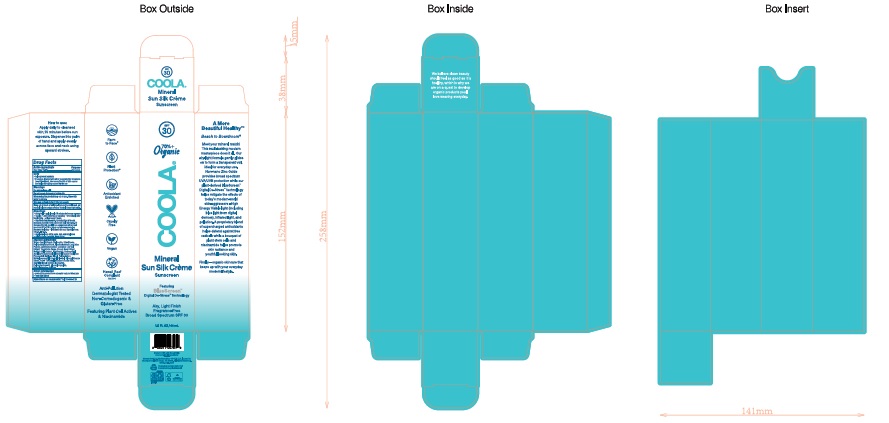 DRUG LABEL: COOLA Mineral Sun Silk Creme Sunscreen
NDC: 79753-070 | Form: LOTION
Manufacturer: COOLA LLC
Category: otc | Type: HUMAN OTC DRUG LABEL
Date: 20241227

ACTIVE INGREDIENTS: ZINC OXIDE 158 mg/1 mL
INACTIVE INGREDIENTS: WATER; COCOA; SCHINUS MOLLE FRUITING TOP; POLYISOBUTYLENE (1000 MW); POLYHYDROXYSTEARIC ACID (2300 MW); NIACINAMIDE; METHYLPROPANEDIOL; JASMINUM SAMBAC FLOWER; MEDIUM-CHAIN TRIGLYCERIDES; BUTYLENE GLYCOL; SORBITAN ISOSTEARATE; PROPANEDIOL; DIDECYLDIMONIUM CHLORIDE; ALOE VERA LEAF; HYDROXYETHYL ACRYLATE/SODIUM ACRYLOYLDIMETHYL TAURATE COPOLYMER (45000 MPA.S AT 1%); DIMETHICONE; CAPRYLYL GLYCOL; CETOSTEARYL ALCOHOL; GLYCERYL CAPRYLATE; GLYCERYL STEARATE CITRATE; PEG-7 TRIMETHYLOLPROPANE COCONUT ETHER; POLYQUATERNIUM-80

COOLA Mineral Sun Silk Crème Sunscreen SPF 30

DRUG FACTS

Active ingredients

Zinc Oxide 15.8%

Purpose

Sunscreen

Uses

Helps prevent sunburn

If used as directed with other sun protection measures (See Directions), decreases the risk of skin cancer and early skin aging cause by the sun.

Warnings

For external use only

Do not use on damaged or broken skin

When using this product keep out of eyes. Rinse with water to remove.

Stop use and ask doctor if skin rash occurs

Keep out of reach of children. If prodcut is swallowed, get medical help or contact Poison Control Center right away.

When using this product keep out of eyes. Rinse with water to remove

Stop use and ask doctor if skin rash occurs

Keep out of reach of children. If product is swallowed, get medical help or contact a Poison Control Center right away.

DOSAGE AND ADMINISTRATION

Inactive ingredients

Water, Caprylic/Capric Triglyceride, Dimethicone,
Polyhydroxystearic Acid, Aloe Barbadensis Leaf Juice
Powder, Jasminum Sambac (Jasmine) Leaf Cell
Extract, Theobroma Cacao (Cocoa) Seed Extract,
Schinus Molle Extract, Niacinamide, Hydroxyethyl
Acrylate/Sodium Acryloyldimethyl Taurate Copolymer,
Propanediol, Butylene Glycol, Polyisobutene,
Methylpropanediol, Cetearyl Alcohol, Glyceryl Stearate
Citrate, PEG-7 Trimethylolpropane Coconut Ether,
Caprylyl Glycol, Sorbitan Isostearate,
Polyquaternium-80, Glyceryl Caprylate,
Didecyldimonium Chloride

Inactive ingredients

Water, Caprylic/Capric Triglyceride, Dimethicone,
Polyhydroxystearic Acid, Aloe Barbadensis Leaf Juice
Powder, Jasminum Sambac (Jasmine) Leaf Cell
Extract, Theobroma Cacao (Cocoa) Seed Extract,
Schinus Molle Extract, Niacinamide, Hydroxyethyl
Acrylate/Sodium Acryloyldimethyl Taurate Copolymer,
Propanediol, Butylene Glycol, Polyisobutene,
Methylpropanediol, Cetearyl Alcohol, Glyceryl Stearate
Citrate, PEG-7 Trimethylolpropane Coconut Ether,
Caprylyl Glycol, Sorbitan Isostearate,
Polyquaternium-80, Glyceryl Caprylate,
Didecyldimonium Chloride

Other information

* protect this product from excessive heat and direct sun

Questions or comments? Call 760-940-2125

How to use:

Apply daily to cleansed skin,

15 minutes before sun exposure.

Dispense into palm of hand and

apply evenly across face and

neck using upward strokes,

QUESTIONS

Questionsor Comments? Call 760-940-2125

Package Labeling

SPF

30

COOLA

MINERAL SUN SILK CREME

SUNSCREEN SPF 30

1.5 FL OZ /44 mL

©2021 COOLA. Distributed by: COOLA LLC, located in

Sunny & Cool San Diego, CA 92010. All Rights Reserved.

res